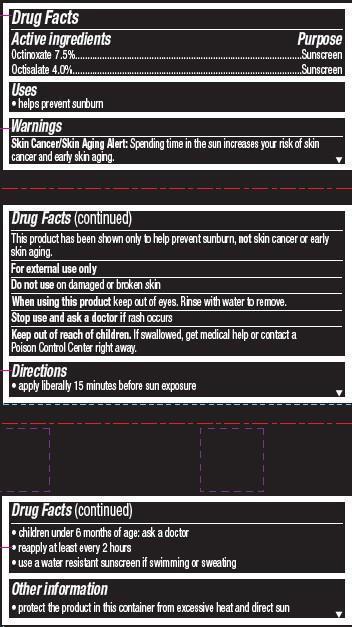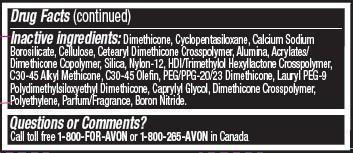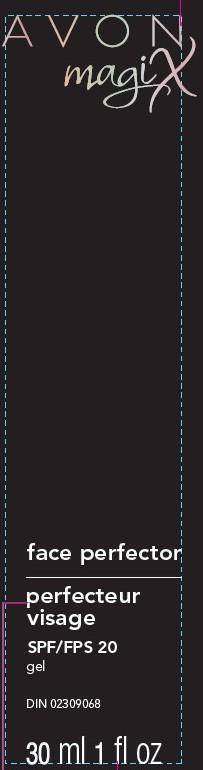 DRUG LABEL: Magix
NDC: 10096-0306 | Form: LOTION
Manufacturer: New Avon LLC
Category: otc | Type: HUMAN OTC DRUG LABEL
Date: 20190101

ACTIVE INGREDIENTS: OCTINOXATE 75 mg/1 mL; OCTISALATE 40 mg/1 mL
INACTIVE INGREDIENTS: WATER

Magix Face Protector

Active ingredients

Octinoxate 7.5%................

Octisalate 4.0%.................

Purpose

..................................Sunscreen
..................................Sunscreen

Uses

• helps prevent sunburn

Warnings
Skin Cancer/Skin Aging Alert: Spending time in the sun increases your risk of skin cancer and early skin aging.This product has been shown only to help prevent sunburn, not skin cancer or early skin aging.

For external use only

Do not use on damaged or broken skin

When using this product keep out of eyes. Rinse with water to remove.

Stop use and ask a doctor if rash occurs

Keep out of reach of children. If swallowed, get medical help or contact a Poison Control Center right away.

Directions

• apply liberally 15 minutes before sun exposure

• children under 6 months of age: ask a doctor
• reapply at least every 2 hours
• use a water resistant sunscreen if swimming or sweating

Other information
• protect the product in this container from excessive heat and direct sun

INACTIVE INGREDIENT

Inactive ingredients: Dimethicone, Cyclopentasiloxane, Calcium Sodium Borosilicate, Cellulose, Cetearyl Dimethicone Crosspolymer, Alumina, Acrylates/Dimethicone Copolymer, Silica, Nylon-12, HDI/Trimethylol Hexyllactone Crosspolymer, C30-45 Alkyl Methicone, C30-45 Olefin, PEG/PPG-20/23 Dimethicone, Lauryl PEG-9 Polydimethylsiloxyethyl Dimethicone, Caprylyl Glycol, Dimethicone Crosspolymer, Polyethylene, Parfum/Fragrance, Boron Nitride, Hydrated Silica, Water/Eau, Tocopherol, Polygonum Multiflorum Root Extract, Rosa Centifolia Flower Extract.

Questions or Comments?
Call toll free 1-800-FOR-AVON or 1-800-265-AVON in Canada